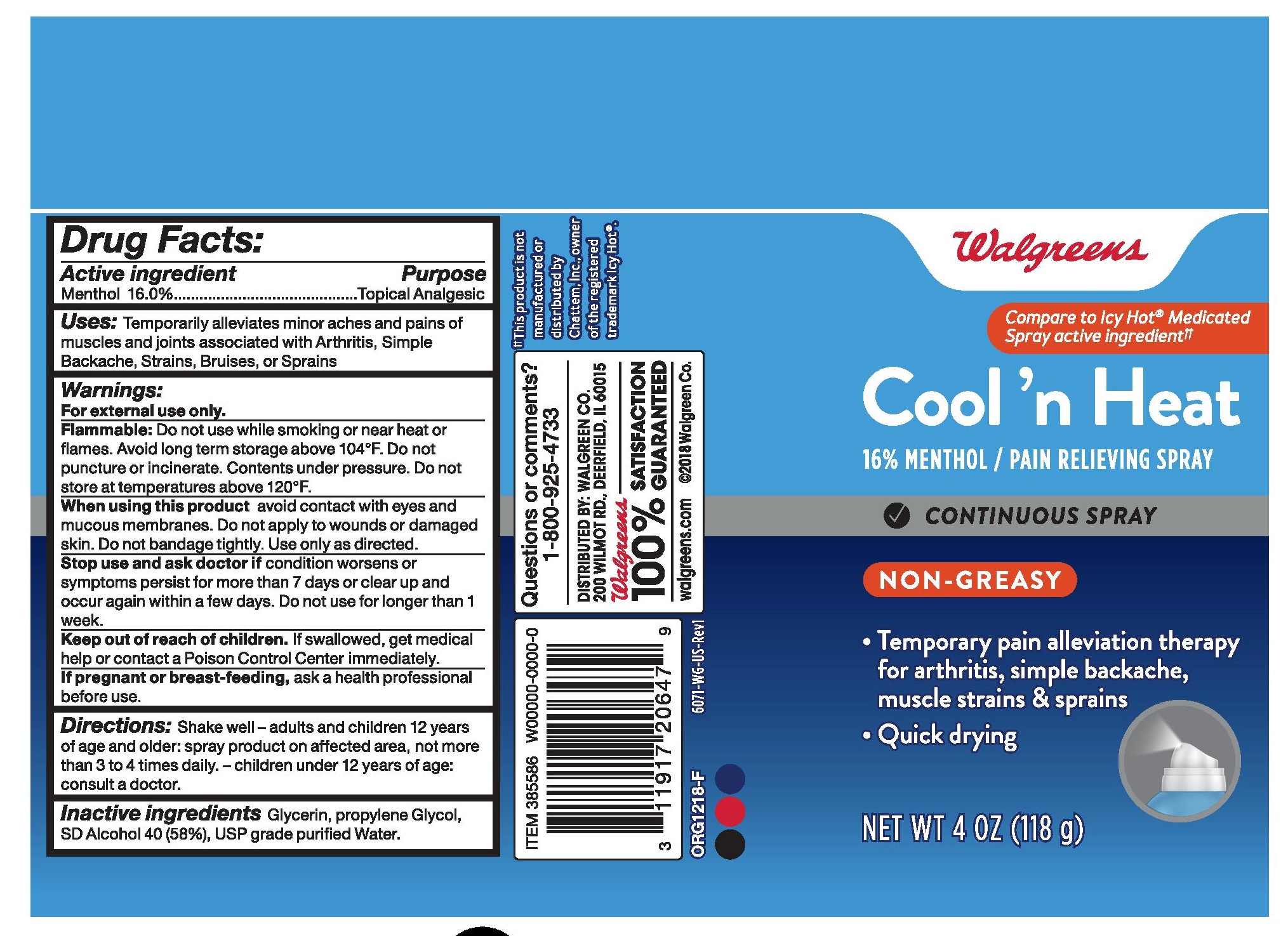 DRUG LABEL: Cool n Heat
NDC: 13709-311 | Form: SPRAY
Manufacturer: NeilMed Pharmaceuticals, Inc.
Category: otc | Type: HUMAN OTC DRUG LABEL
Date: 20240111

ACTIVE INGREDIENTS: MENTHOL 160 mg/1 mL
INACTIVE INGREDIENTS: GLYCERIN; PROPYLENE GLYCOL

Cool n Heat

ACTIVE INGREDIENT PURPOSE

Menthol 16% Topical analgesic

Uses

Temporality alleviates minor aches and pains of muscles and joints associated with Arthritis, Simple Backache, Strains, Bruises, or Sprains

Warnings:

For external use only.
Flammable: Do not use while smoking or near heat or flames. Avoid long term storage
above 104°F. Do not puncture or incinerate. Contents under pressure. Do not store at temperatures above 120°F.
When using this product avoid contact with eyes and mucous membranes. Do not apply to wounds or damaged skin. Do not bandage tightly. Use only as directed.
Stop use and ask doctor if condition worsens or symptoms persist for more than 7 days or clear up and occur again within a few days. Do not use for longer than 1 week.
Keep out of reach of children. If swallowed, get medical help or contact a Poison Control Center immediately.
If pregnant or breast-feeding, ask a health professional before use.

Directions:

Shake well – adults and children 12 year of age and older: spray product on affected area, not more than 3 to 4 times daily. – children under 12 years of age: consult a doctor.

Inactive ingredients:

Glycerin, propylene Glycol, SD Alcohol 40 (58%), USP grade purified Water.

Dosage and Administration

Shake well
adults and children 12 years of age and older spray on affected area not more than 3 to 4 times daily

children under 12 years of age consult a doctor

Indication & Usage

temporarily relief of pain and itching associated with

arthritis simple backache muscle strains bruises cramps muscle sprains

OTC - Keep Out of Reach of Children

Keep out of reach of the children. If swallowed, get medical help or contact a Poison Control Center right away

If pregnant or breast-feeding, ask a health professional before use.

OTC Purpose Section

temporarily relief of pain and itching associated with:

arthritis • simple backache • muscle strains • bruises • cramps • muscle sprains